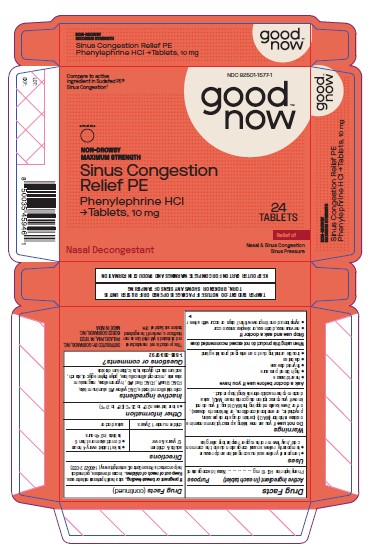 DRUG LABEL: Sinus Congestion Relief
NDC: 82501-1577 | Form: TABLET, COATED
Manufacturer: Gobrands, Inc
Category: otc | Type: HUMAN OTC DRUG LABEL
Date: 20241220

ACTIVE INGREDIENTS: PHENYLEPHRINE HYDROCHLORIDE 10 mg/1 1
INACTIVE INGREDIENTS: SILICON DIOXIDE; D&C YELLOW NO. 10 ALUMINUM LAKE; FD&C BLUE NO. 1; FD&C RED NO. 40; HYPROMELLOSES; MAGNESIUM STEARATE; CELLULOSE, MICROCRYSTALLINE; POLYETHYLENE GLYCOL, UNSPECIFIED; STARCH, POTATO; SODIUM STARCH GLYCOLATE TYPE A POTATO; TALC; TITANIUM DIOXIDE

Sinus Congestion Relief

Active Ingredient (in each tablet)

Phenylephrine HCl 10 mg

Purpose

Nasal decongestant

Uses

• temporarily relieves sinus congestion and pressure • temporarily relieves nasal congestion due to the common cold, hay fever or other upper respiratory allergies

Warnings

Do not use if you are now taking a prescription monoamine oxidase inhibitor (MAOI) (certain drugs for depression, psychiatric, or emotional conditions, or Parkinson’s disease), or for 2 weeks after stopping the MAOI drug. If you do not know if your prescription drug contains an MAOI, ask a doctor or pharmacist before taking this product.

Ask a doctor before use if you have • heart disease • high blood pressure • thyroid disease • diabetes
• trouble urinating due to an enlarged prostate gland

When using this product do not exceed recommended dose

Stop use and ask a doctor if • nervousness, dizziness, or sleeplessness occur • symptoms do not improve within 7 days or occur with a fever

PREGNANCY OR BREAST FEEDING

If pregnant or breast-feeding, ask a health professional before use.

Keep out of reach of children. In case of overdose, get medical help or contact a Poison Control Center right away. (1-800-222-1222)

Directions

adults & children 12 years & over | - take 1 tablet every 4 hours - do not take more than 6 tablets in 24 hours
children under 12 years | ask a doctor

Other information

• store between 20-25°C (68-77°F)

Inactive ingredients

colloidal silicon dioxide, D&C yellow#10 aluminum lake, FD&C Blue#1, FD&C Red #40, hypromellose, magnesium stearate, microcrytalline cellulose, polyethylene glycol, starch, sodium starch glycolate, talc, titanium dioxide

Questions or comments?

1-888-333-9792

PRINCIPAL DISPLAY PANEL

Compare to active
ingredient in Sudafed PE®
Sinus Congestion†

NDC 82501-1577-1

Good now

Sinus Congestion Relief PE
Phenylephrine HCl Tablets, 10 mg

24 TABLETS

Nasal Decongestant

Relief of
Nasal & Sinus Congestion
Sinus Pressure